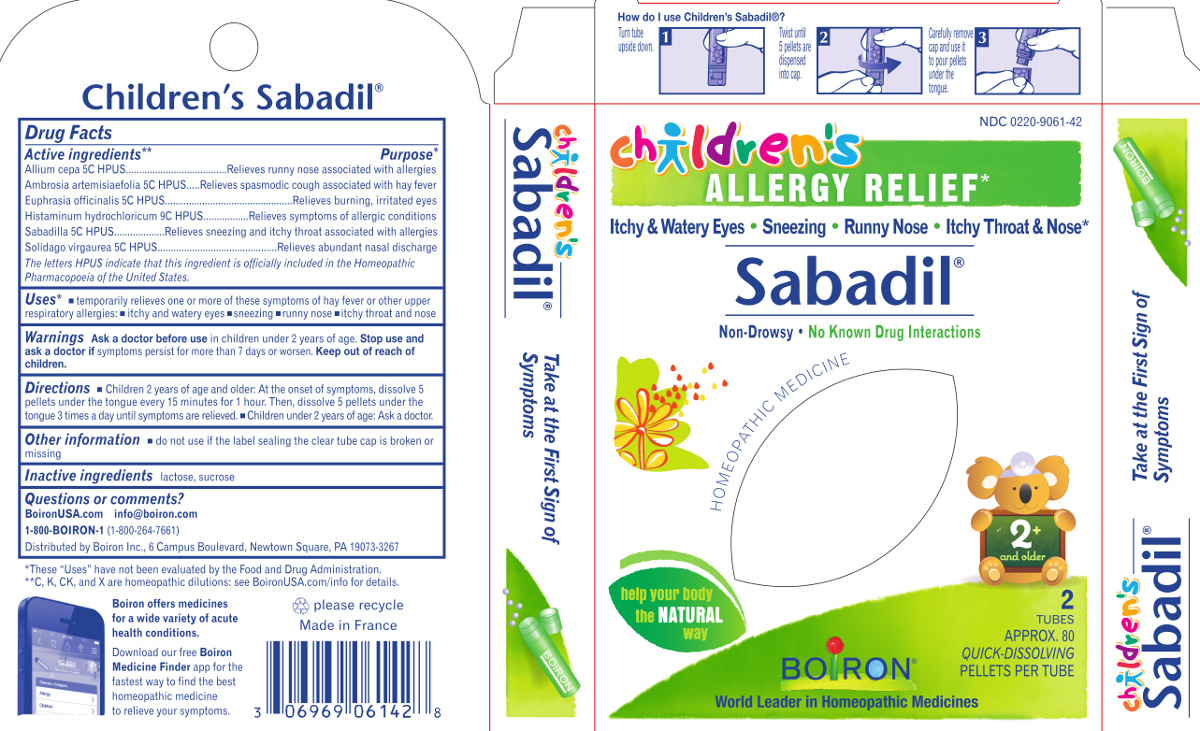 DRUG LABEL: Childrens Sabadil
NDC: 0220-9061 | Form: PELLET
Manufacturer: Laboratoires Boiron
Category: homeopathic | Type: HUMAN OTC DRUG LABEL
Date: 20201102

ACTIVE INGREDIENTS: ONION 5 [hp_C]/1 1; AMBROSIA ARTEMISIIFOLIA 5 [hp_C]/1 1; HISTAMINE DIHYDROCHLORIDE 9 [hp_C]/1 1; SCHOENOCAULON OFFICINALE SEED 5 [hp_C]/1 1; EUPHRASIA STRICTA 5 [hp_C]/1 1; SOLIDAGO VIRGAUREA FLOWERING TOP 5 [hp_C]/1 1
INACTIVE INGREDIENTS: SUCROSE; LACTOSE

Childrens Sabadil

Active Ingredients**

Allium cepa 5C HPUS
Ambrosia artemisiaefolia 5C HPUS
Euphrasia officinalis 5C HPUS
Histaminum hydrochloricum 9C HPUS
Sabadilla 5C HPUS
Solidago virgaurea 5C HPUS
The letters HPUS indicate that this ingredient is officially included in the Homeopathic Pharmacopoeia of the United States.

Purpose*

Allium cepa 5C HPUS ..... Relieves runny nouse associated with allergies
Ambrosia artemisiaefolia 5C HPUS ..... Relieves spasmodic cough associated with hay fever
Histaminum hydrochloricum 9C HPUS ..... Relieves symptoms of allergic conditions
Euphrasia officinalis 5C HPUS ..... Relieves burning, irritated eyes
Sabadilla 5C HPUS ..... Relieves sneezing associated with allergies
Solidago virgaurea 5C HPUS ..... Relieves abundant nasal discharge

Uses*

temporarily relieves on or more of these symptoms of hay fever or other uppper respiratory allergies:
itchy and watery eyes
sneezing
runny nose
itchy throat and nose

Warnings

Ask a doctor before use in children under 2 years of age.

Stop use and ask a doctor if

symptoms persist for more than 7 days or worsen.

Directions

Children 2 years of age and older: At the onser of symptoms, dissolve 5 pellets under the tounge every 15 minutes for 1 hour. Then, dissolve 5 pellets under the tounge 3 times a day until symptoms are releived.
Children under 2 years of age: Ask a doctor.

Other information

do not use if the label sealing the clear tube cap is broken or missing

Inactive ingredients

lactose, sucrose

Questions, Comments?

BoironUSA.com
info@boiron.com
1-800-BOIRON-1 (1-800-264-7661)
Distributed by Boiron Inc., 6 Campus Boulevard, Newtown Square, PA 19073-3267

Notes:

*These "Uses" have not been evaluated by the Food And Drug Administration.
**C, K, CK and X are homeopathic dilutions: see BoironUSA.com/info for details.